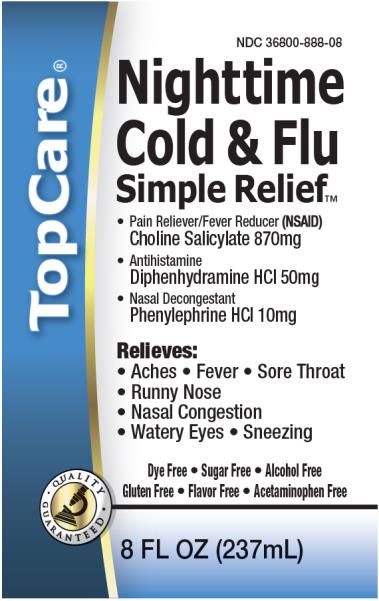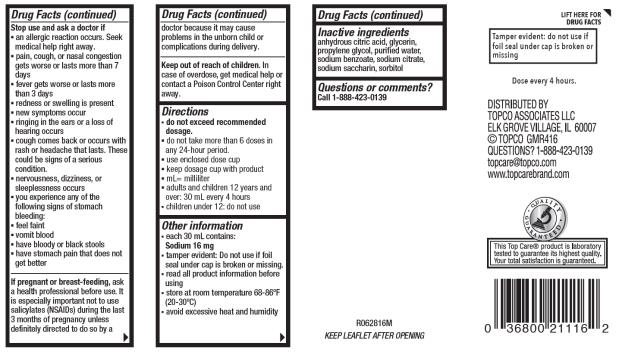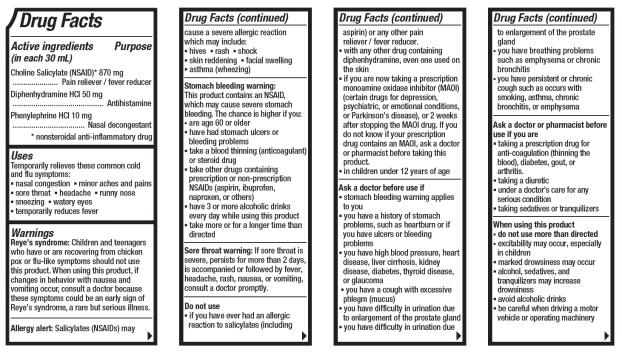 DRUG LABEL: TopCare Nighttime Cold and Flu Simple Relief
NDC: 36800-888 | Form: LIQUID
Manufacturer: TOPCO ASSOCIATES LLC
Category: otc | Type: HUMAN OTC DRUG LABEL
Date: 20180628

ACTIVE INGREDIENTS: CHOLINE SALICYLATE 870 mg/1 mL; DIPHENHYDRAMINE HYDROCHLORIDE 50 mg/1 mL; PHENYLEPHRINE HYDROCHLORIDE 10 mg/1 mL
INACTIVE INGREDIENTS: ANHYDROUS CITRIC ACID; GLYCERIN; PROPYLENE GLYCOL; WATER; SODIUM BENZOATE; SODIUM CITRATE; SACCHARIN SODIUM; SORBITOL

TOP CARE NIGHTTIME COLD AND FLU SIMPLE RELIEF

TopCare Nighttime Cold & Flu Simple Relief

(choline salicylate, diphenhydramine hcI, phenylephrine hcl), solution

Topco Associates LLC

--

Topco Associates LLC. Nighttime Cold & Flu Simple Relief

Drug Facts

Active ingredients (in each 30 mL)

Choline Salicylate (NSAID)* 870 mg

Diphenhydramine HCI 50mg

Phenylephrine HCl 10 mg

Purpose

Pain reliever/fever reducer

Antihistamine

Nasal decongestant

nonsteroidal anti-inflammatory drug*

Uses

temporarily relieves these common cold and flu symptoms:

▪ nasal congestion

▪ minor aches and pains

▪ runny nose

▪ sneezing

▪ watery eyes

▪ sore throat

▪ headache

▪ temporarily reduces fever

Warnings

Reye's syndrome

Children and teenagers who have or are recovering from chicken pox or flu-like symptoms should not use this product. When using this product, if changes in behavior with nausea and vomiting occur, consult a doctor because these symptoms could be an early sign of Reye's syndrome, a rare but serious illness.

Allergy alert

Salicylates (NSAIDs) may cause a severe allergic reaction which may include:

▪ hives

▪ rash

▪ shock

▪ skin reddening

▪ facial swelling ▪ asthma (wheezing)

Stomach bleeding warnings

This product contains an NSAID, which may cause severe stomach bleeding. The chance is higher if you:

▪ are age 60 or older

▪ have had stomach ulcers or bleeding problems

▪ take a blood thinning (anticoagulant) or steroid drug

▪ take other drugs containing prescription or non-prescription NSAIDs (aspirin, ibuprofen, naproxen, or others)

▪ have 3 or more alcoholic drinks every day while using this product

▪ take more or for a longer time than directed

Sore throat warning

If sore throat is severe, persists for more than 2 days, is accompanied or followed by fever, headache, rash, nausea, or vomiting, consult a doctor promptly.

Do not use

▪ if you have ever had an allergic reaction to salicylates (including aspirin) or any other pain reliever / fever reducer.

▪ with any other drug containing diphenhydramine, even one used on the skin

▪ if you are now taking a prescription monoamine oxidase inhibitor (MAOI) (certain drugs for depression, psychiatric, or emotional conditions, or Parkinson’s disease), or 2 weeks after stopping the MAOI drug. If you do not know if your prescription drug contains an MAOI, ask a doctor or pharmacist before taking this product.

▪ in children under 12 years of age

Ask a doctor before use if

▪ stomach bleeding warning applies to you

▪ you have a history of stomach problems, such as heartburn or if you have ulcers or bleeding problems

▪ you have high blood pressure, heart disease, liver cirrhosis, kidney disease, diabetes, thyroid disease, or glaucoma

▪ you have a cough with excessive phlegm (mucus)

▪ you have difficulty in urination due to enlargement of the prostate gland

▪ you have breathing problems such as emphysema or chronic bronchitis

▪ you have a persistent or chronic cough such as occurs with smoking, asthma, chronic bronchitis, or emphysema

Ask a doctor or pharmacist before use if you are

▪ taking a prescription drug for anticoagulation (thinning the blood), diabetes, gout, or arthritis.

▪ taking a diuretic

▪ under a doctor’s care for any serious condition

▪ taking sedatives or tranquilizers

When using this product

▪ do not use more than directed

▪ excitability may occur, especially in children

▪ marked drowsiness may occur

▪ alcohol, sedatives, and tranquilizers may increase drowsiness

▪ avoid alcoholic drinks

▪ be careful when driving a motor vehicle or operating machinery

Stop use and ask a doctor if

▪ an allergic reaction occurs. Seek medical help right away.

▪ pain, cough, or nasal congestion gets worse or lasts more than 7 days

▪ fever gets worse or lasts more than 3 days

▪ redness or swelling is present

▪ new symptoms occur

▪ ringing in the ears or a loss of hearing occurs

▪ cough comes back or occurs with rash or headache that lasts. These could be signs of a serious condition.

▪ nervousness, dizziness, or sleeplessness occurs

▪ you experience any of the following signs of stomach bleeding:

▪ feel faint

▪ vomit blood

▪ have bloody or black stools

▪ have stomach pain that does not get better

If pregnant or breast-feeding,

ask a health professional before use. It is especially important not to use salicylates (NSAIDs) during the last 3 months of pregnancy unless definitely directed to do so by a doctor because it may cause problems in the unborn child or complications during delivery.

Keep out of reach of children.

In case of overdose, get medical help or contact a Poison Control Center right away.

Directions

- do not exceed recommended dosage.
- do not take more than 6 doses in any 24-hour period.
- use enclosed dose cup
- keep dosage cup with product
- mL = milliliters
- adults and children 12 years of age and over: 30mL every 4 hours
- children under 12 years of age: do not use

Other information

- each 30mL contains: Sodium 16 mg
- tamper evident: Do not use if foil seal under cap is broken or missing.
- read all product information before using
- store at 68° to 86°F (20° to 30°C)
- avoid excessive heat and humidity

Inactive ingredients

citric acid anhydrous, glycerin, propylene glycol, purified water, sodium benzoate, sodium citrate, sodium saccharin, sorbitol

Questions or Comments?

Call 1-888-423-0139

PRINCIPAL DISPLAY PANEL

NDC 36800-888-08
Nighttime
Cold & Flu
Simple Relief
8 FL OZ (237mL)